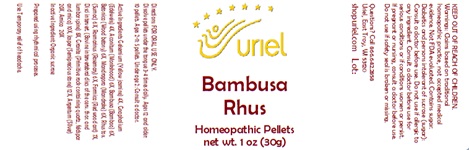 DRUG LABEL: Bambusa Rhus
NDC: 48951-2017 | Form: PELLET
Manufacturer: Uriel Pharmacy Inc.
Category: homeopathic | Type: HUMAN OTC DRUG LABEL
Date: 20241213

ACTIVE INGREDIENTS: GELSEMIUM SEMPERVIRENS ROOT 4 [hp_X]/1 1; PSEUDOGNAPHALIUM LUTEOALBUM LEAF 4 [hp_X]/1 1; ACONITUM NAPELLUS 6 [hp_X]/1 1; BAMBUSA VULGARIS WHOLE 6 [hp_X]/1 1; STACHYS OFFICINALIS 6 [hp_X]/1 1; MANDRAGORA OFFICINARUM ROOT 6 [hp_X]/1 1; TOXICODENDRON PUBESCENS LEAF 6 [hp_X]/1 1; ROSMARINUS OFFICINALIS FLOWERING TOP 6 [hp_X]/1 1; FORMICA RUFA 7 [hp_X]/1 1; BOS TAURUS INTERVERTEBRAL DISC 8 [hp_X]/1 1; PENOXSULAM 10 [hp_X]/1 1; SILICON DIOXIDE 12 [hp_X]/1 1; SILVER 20 [hp_X]/1 1; ARNICA MONTANA 20 [hp_X]/1 1
INACTIVE INGREDIENTS: SUCROSE

Bambusa Rhus

INDICATIONS AND USAGE

Directions: FOR ORAL USE ONLY.

DOSAGE AND ADMINISTRATION

Dissolve pellets under the tongue 3-4 times daily. Ages 12 and older: 10 pellets. Ages 2-11: 5 pellets. Under age 2: Consult
a doctor.

ACTIVE INGREDIENT

Active Ingredients: Gelsemium (Yellow jasmine) 4X, Gnaphalium (Edelweiss) 4X, Aconitum (Monkshood) 6X, Bambusa (Bamboo) 6X, Betonica (Wood betony) 6X, Mandragora (Mandrake) 6X, Rhus tox. (Sumac) 6X, Rosmarinus (Rosemary) 6X, Formica (Red wood ant) 7X, Disci intervert. (Bovine intervertebral discs of the cerv. thor. and lumbar spine) 8X, Granite (Primitive rock containing quartz, feldspar and mica) 10X, Jasper (Semiprecious stone) 12X, Argentum (SIlver) 20X, Arnica 20X

Inactive Ingredient: Sucrose

Prepared using rhythmical processes.

PURPOSE

Use: Temporary relief of headache.

KEEP OUT OF REACH OF CHILDREN.

WARNINGS

Warnings: Claims based on traditional homeopathic practice, not accepted medical evidence. Not FDA evaluated. Contains sugar. Diabetics and persons intolerant of sucrose (sugar): Consult a doctor before use. Do not use if allergic to any ingredient. Consult a doctor before use for serious conditions or if conditions worsen or persist. If pregnant or nursing, consult a doctor before use. Do not use if safety seal is broken or missing.

Questions? Call 866.642.2858
Uriel, East Troy, WI 53120
shopuriel.com Lot: